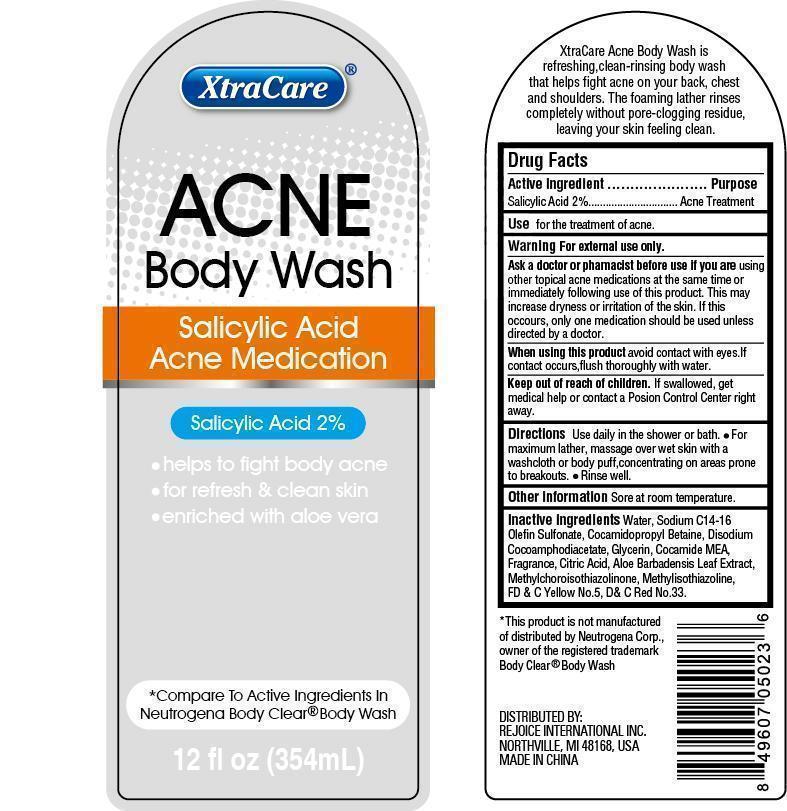 DRUG LABEL: Acne Body Wash
NDC: 57337-030 | Form: GEL
Manufacturer: Rejoice International
Category: otc | Type: HUMAN OTC DRUG LABEL
Date: 20240228

ACTIVE INGREDIENTS: SALICYLIC ACID 7 mg/354 mg
INACTIVE INGREDIENTS: WATER; SODIUM C14-16 OLEFIN SULFONATE; COCAMIDOPROPYL BETAINE; DISODIUM COCOAMPHODIACETATE; GLYCERIN; COCO MONOETHANOLAMIDE; CITRIC ACID MONOHYDRATE; ALOE VERA LEAF; METHYLCHLOROISOTHIAZOLINONE; METHYLISOTHIAZOLINONE; FD&C YELLOW NO. 5; D&C RED NO. 33

Acne Body Wash

Active Ingredient Purpose

Salicylic Acid 2% ............Acne Treatment

PURPOSE

XtraCare

ACNE Body Wash

Salicylic Acid

Acne Medication

- helps to fight body acne
- for refresh & clean skin
- enriched with aloe vera

*Compare to Active Ingredients in Neutrogena Body Clear Body Wash

Keep out of reach of children. If swallowed, get medical help or contact a Poison Control Center right away.

INDICATIONS AND USAGE

XtraCare Acne Body wash is refreshing, clean-rinsing body wash that helps fight acne on your back, chest, and shoulders. The foaming lather rinses completely without pore-clogging residue, leaving your skin feeling clean.

Use

for the treatment of acne.

DOSAGE AND ADMINISTRATION

Directions: Use daily in the shower or bath. For maximum lather, massage over wet skin with a washcloth or body puff, concentrating on areas prone to breakouts. Rinse well.

WARNINGS

Warning: for external use only.

Ask a doctor or pharmacist before use if you are using other topical acne medications at the same time or immediately following use of this product. This may increase dryness or irritation of the skin. If this occurs, only one medication should be used unless directed by a doctor.

When using this product avoid contact with eyes. If contact occurs, flush thoroughly with water.

Other information: Store at room temperature.

*this product is not manufactured of distributed by Neutrogena Corp., owner of the registered trademark Body Clear® Body Wash.

Distributed By:

REJOICE INTERNATIONAL INC.

NORTHVILLE, MI 48168, USA

MADE IN CHINA

INACTIVE INGREDIENT

Inactive Ingredients: water, sodium C14-16 olefin sulfonate, cocamidopropyl betaine, disodium cocoamphodiacetate, glycerin, cocamide MEA, fragrance, citric acid, aloe barbadensis leaf extract, methylchloroisothiazolinone, methylisothiazoline, FD&C yellow no.5, D&C red no.33